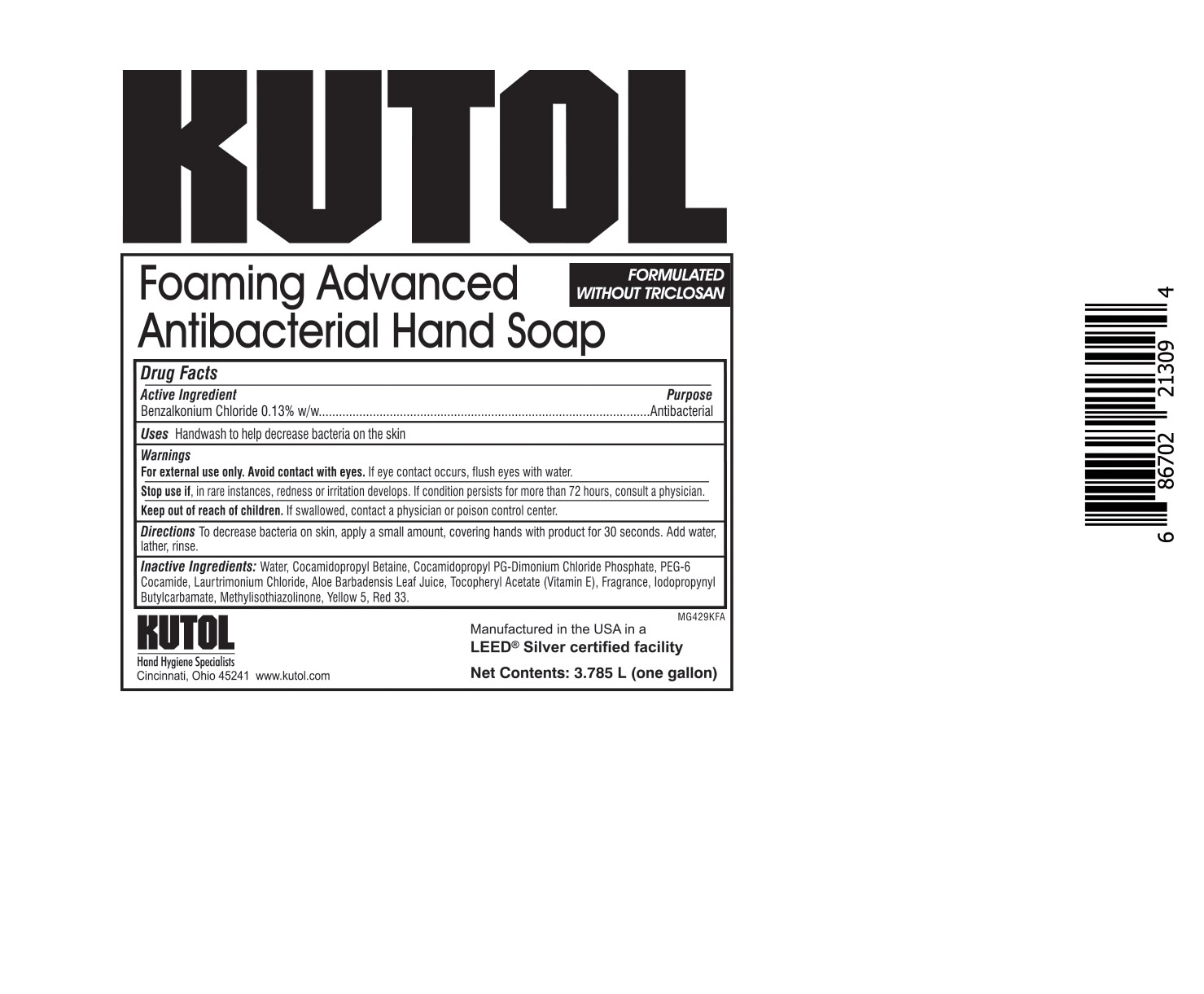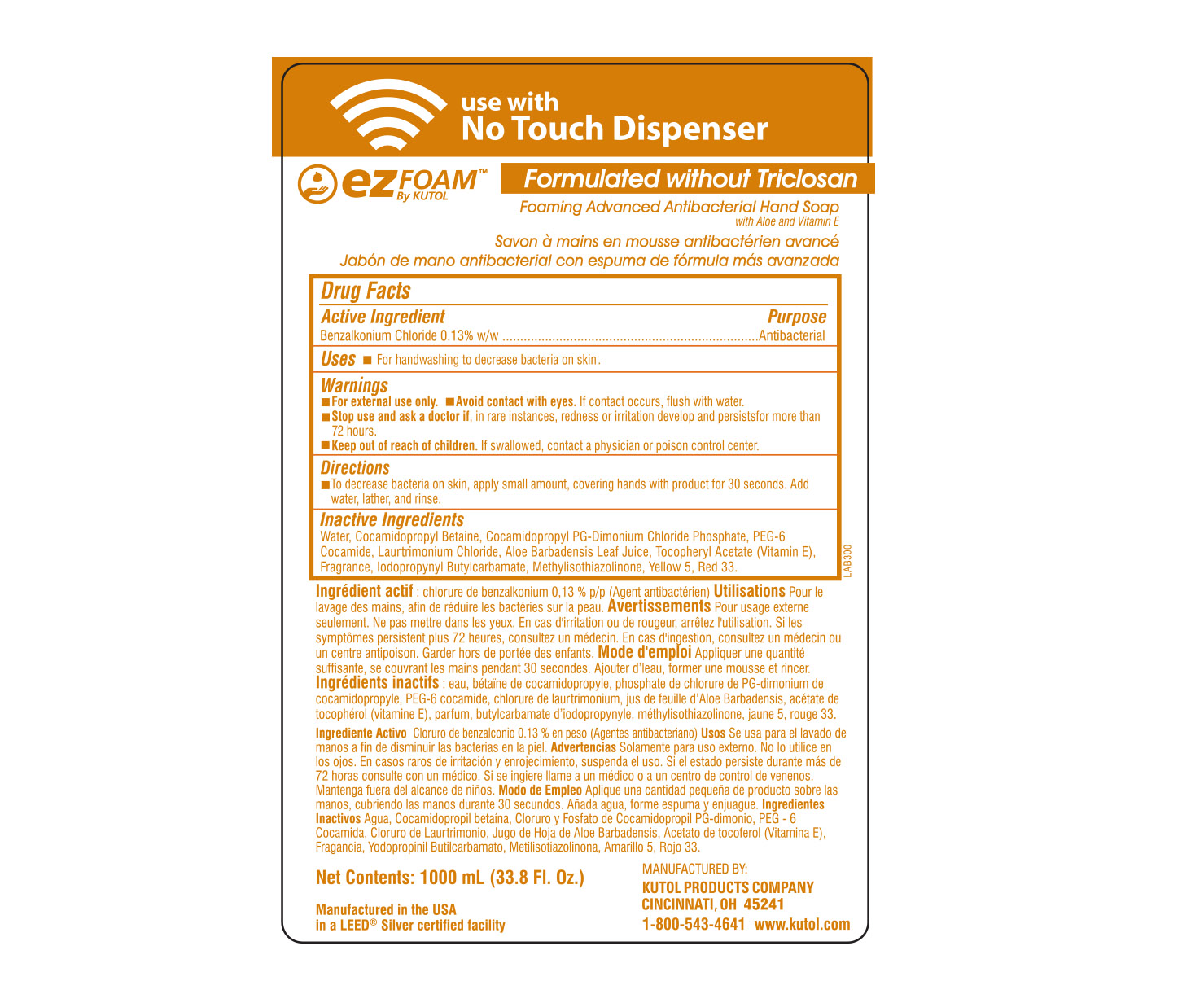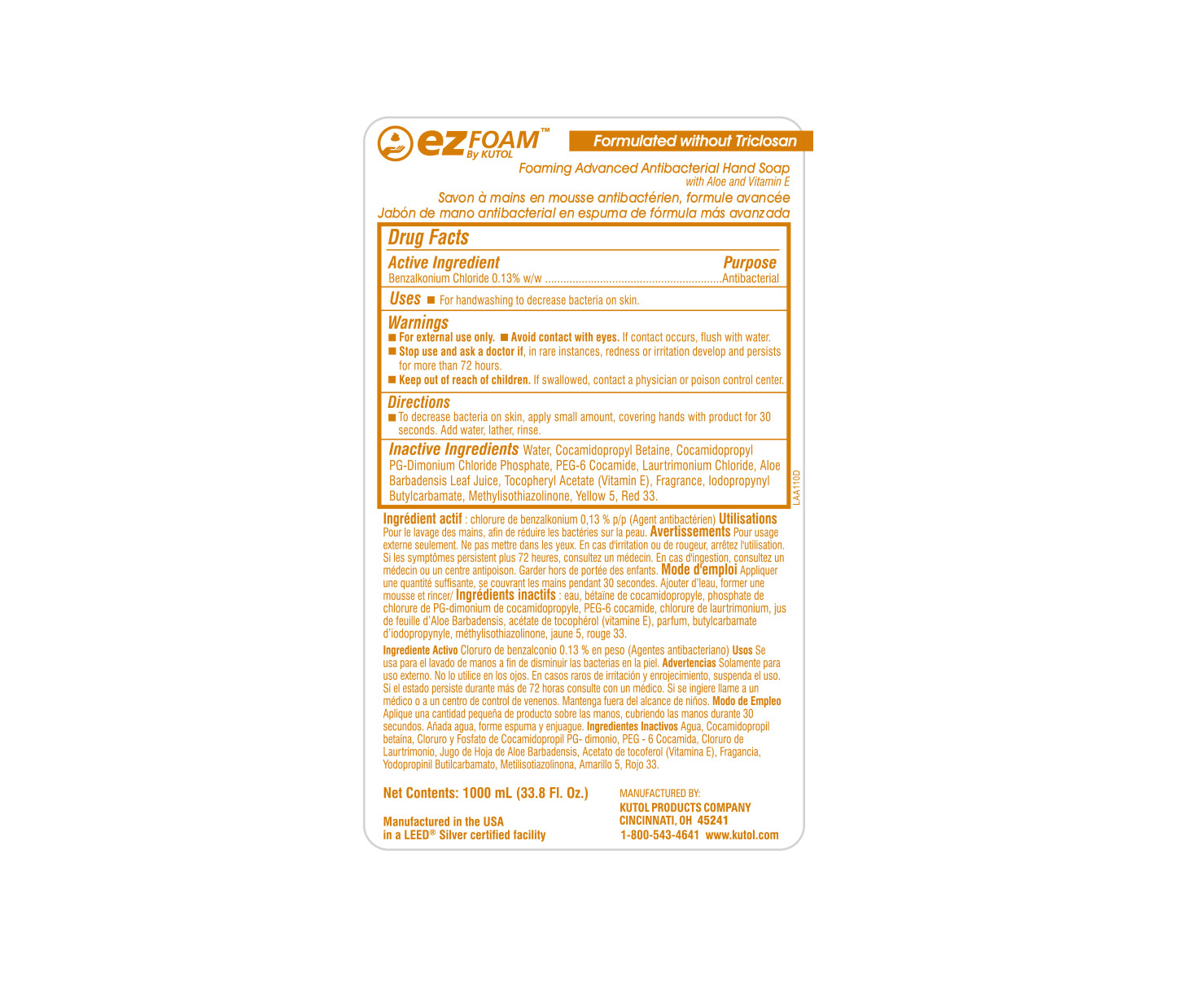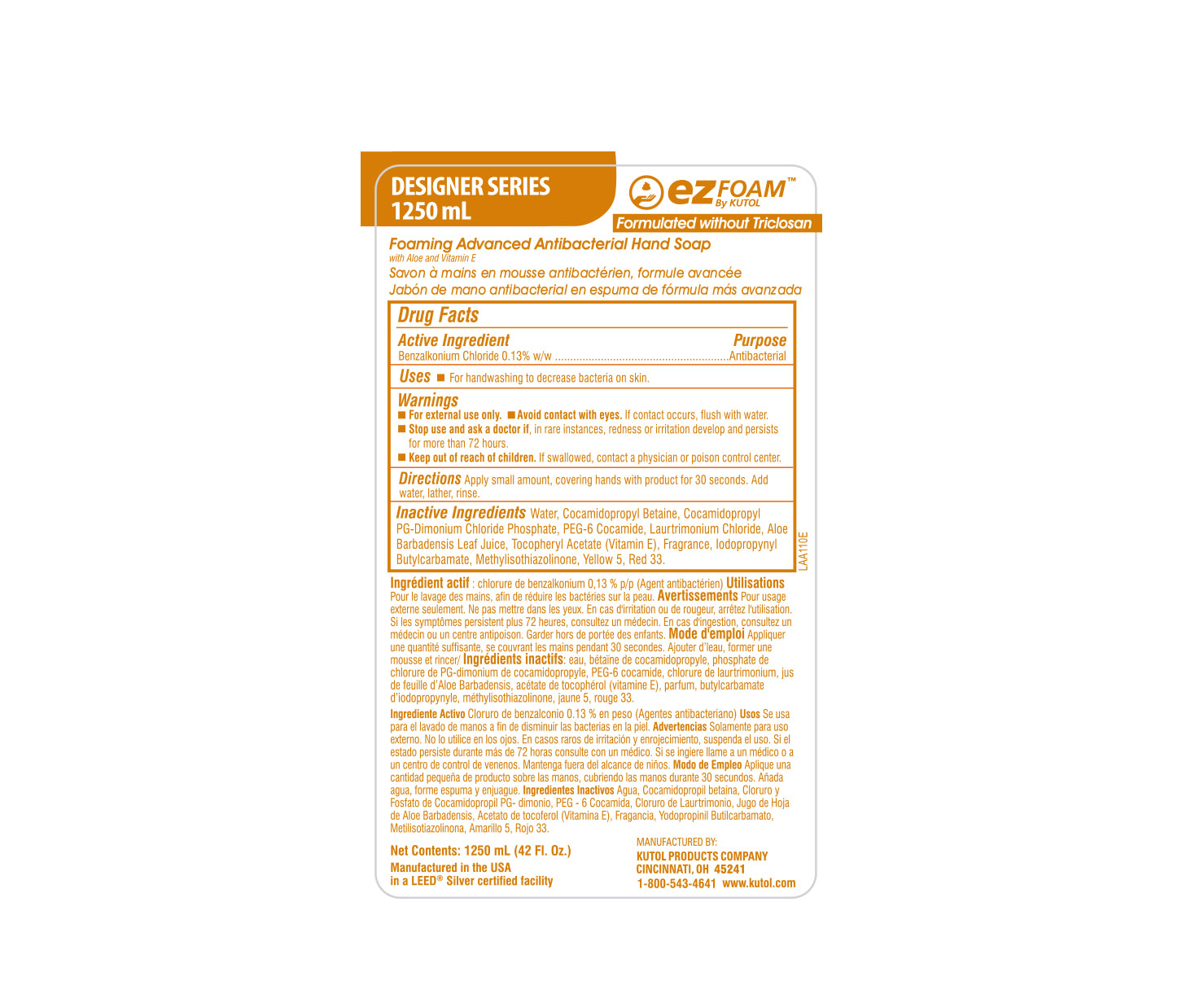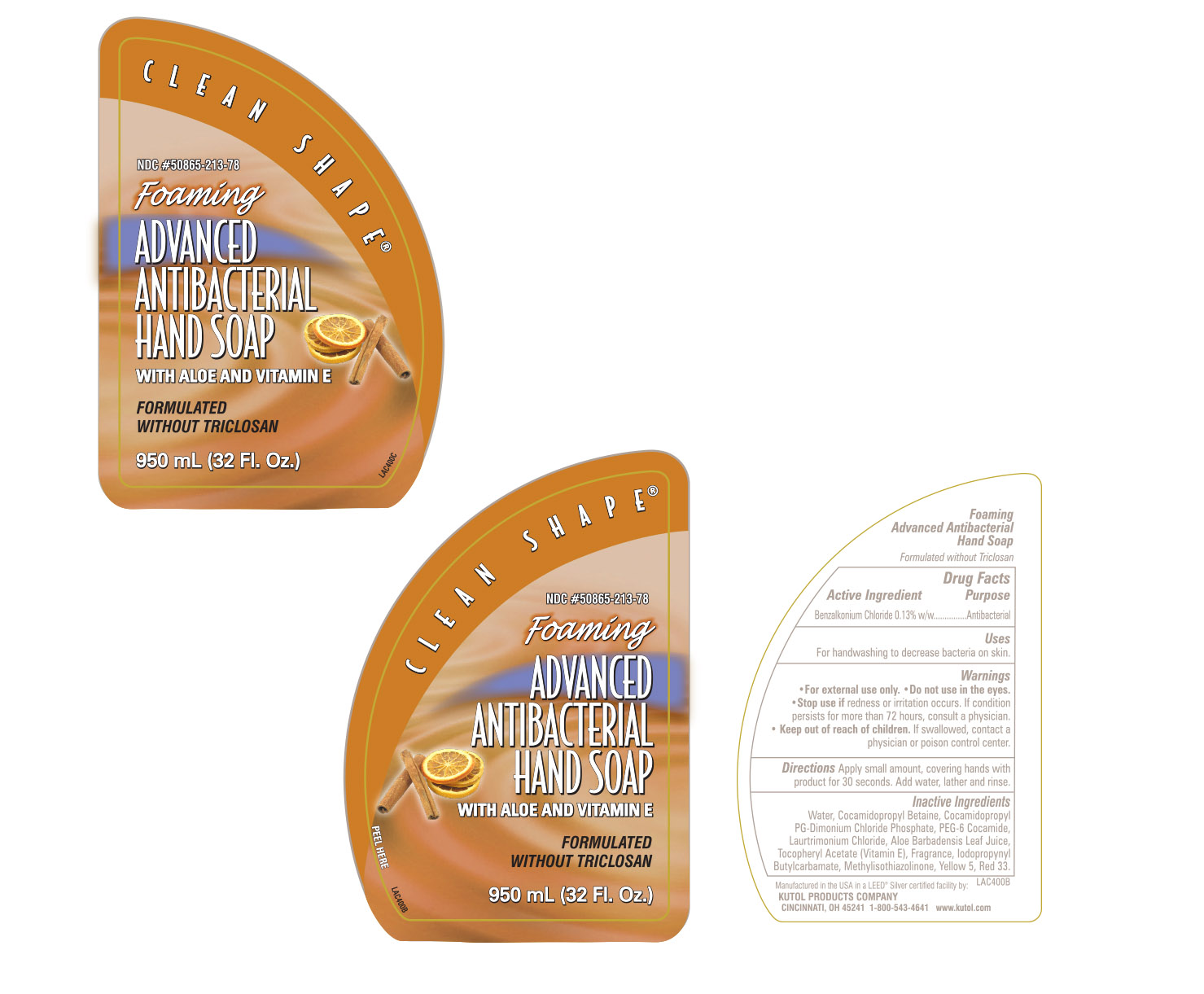 DRUG LABEL: Foaming Advanced Antibacterial Hand
NDC: 50865-213 | Form: SOAP
Manufacturer: Kutol Products Company
Category: otc | Type: HUMAN OTC DRUG LABEL
Date: 20241218

ACTIVE INGREDIENTS: BENZALKONIUM CHLORIDE 0.003 mg/1 mL
INACTIVE INGREDIENTS: WATER; COCAMIDOPROPYL BETAINE; COCAMIDOPROPYL PG-DIMONIUM CHLORIDE PHOSPHATE; PEG-6 COCAMIDE; LAURTRIMONIUM CHLORIDE; METHYLISOTHIAZOLINONE; IODOPROPYNYL BUTYLCARBAMATE; FD&C YELLOW NO. 5; D&C RED NO. 33; ALOE VERA LEAF; .ALPHA.-TOCOPHEROL ACETATE

F213F Foaming advanced antibacterial soap

Active Ingredient

Benzalkonium Chloride 0.13% w/w

Purpose

Antibacterial

Keep out of reach of children. If swallowed, contact a physician or poison control center.

INDICATIONS AND USAGE

Uses Handwash to help decrease bacteria on the skin

DOSAGE AND ADMINISTRATION

Directions To decrease bacteria on the skin, apply a small amount, covering hands with product for 30 seconds. Add water, lather, rinse.

Warnings

For external use only. Avoid contact with eyes. If eye contact occurs, flush eyes with water.

Stop use if, in rare instances, redness or irritation develops. If condition persists for more than 72 hours, consult a physician.

Inactive Ingredients

water, cocamidopropyl betaine, cocamidopropyl PG-dimonium chloride phosphate, PEG-6 cocamide, laurtrimonium chloride, aloe barbadensis leaf juice, tocopheryl acetate (vitamin E), fragrance, iodopropynyl butylcarbamade, methylisothiazolinone, yellow 5, red 33.